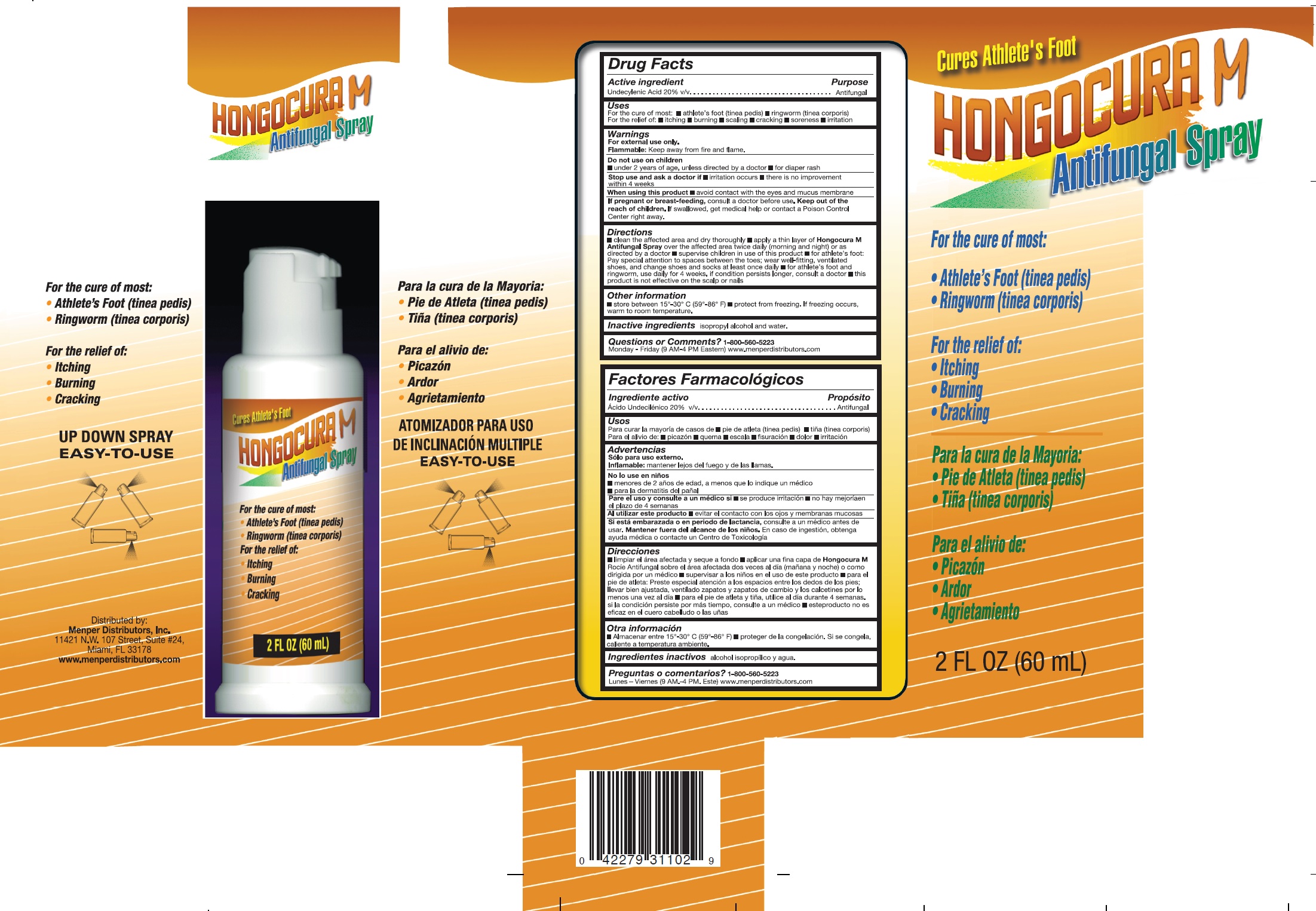 DRUG LABEL: Hongocura
NDC: 53145-219 | Form: SPRAY
Manufacturer: MENPER DISTRIBUTORS, INC.
Category: otc | Type: HUMAN OTC DRUG LABEL
Date: 20250722

ACTIVE INGREDIENTS: UNDECYLENIC ACID 20 mg/100 mL
INACTIVE INGREDIENTS: ISOPROPYL ALCOHOL; WATER

Hongocura M

Active Ingredient Purpose

Undecylenic Acid 20% v/v.................Antifungal

Purpose

- Antifungal

Warnings

For external use only. Flammable: Keep away from fire and flame.

Do not use on children

- Under 2 years of age, unless directed by a doctor
- for diaper rash

Stop use and ask a doctor if

- Irritation occurs
- there is no improvement within 4 weeks

When using this product

- Avoid contact with eyes and mucus membrane

Do not use on children

- Under 2 years of age, unless directed by a doctor
- for diaper rash

Stop use and ask a doctor if

- Irritation occurs
- there is no improvement within 4 weeks

When using this product

- Avoid contact with eyes and mucus membrane

PREGNANCY OR BREAST FEEDING

If pregnant or breast-feeding,consult a doctor before use.

KEEP OUT OF REACH OF CHILDREN

Keep out of the reach of children.If swallowed, get medical help or contact a Posion Control Center right away.

Directions

- clean the affected area and dry throughly
- apply a thin layer of Hongocura M Antifungal Sprayover the affected area twice daily (morning and night) or as directed by a doctor
- supervise children in use of this product
- for athlete's foot: Pay special attention to spaces between the toes; wear well-fitting, ventilated shoes, and change shoes and socks at least once daily
- for athlete's foot and ringworm, use daily for 4 weeks. if condition persists longer, consult a doctor
- this product is not effective on the scalp or nails
- store between 15°-30°C(59°-86°F)

Inactive Ingredients

isopropyl alcohol and water.

QUESTIONS

Questions: 1-800-560-5223 Monday - Friday (9 AM - 4 PM EST) www.menperdistributors.com